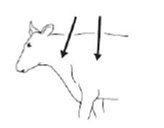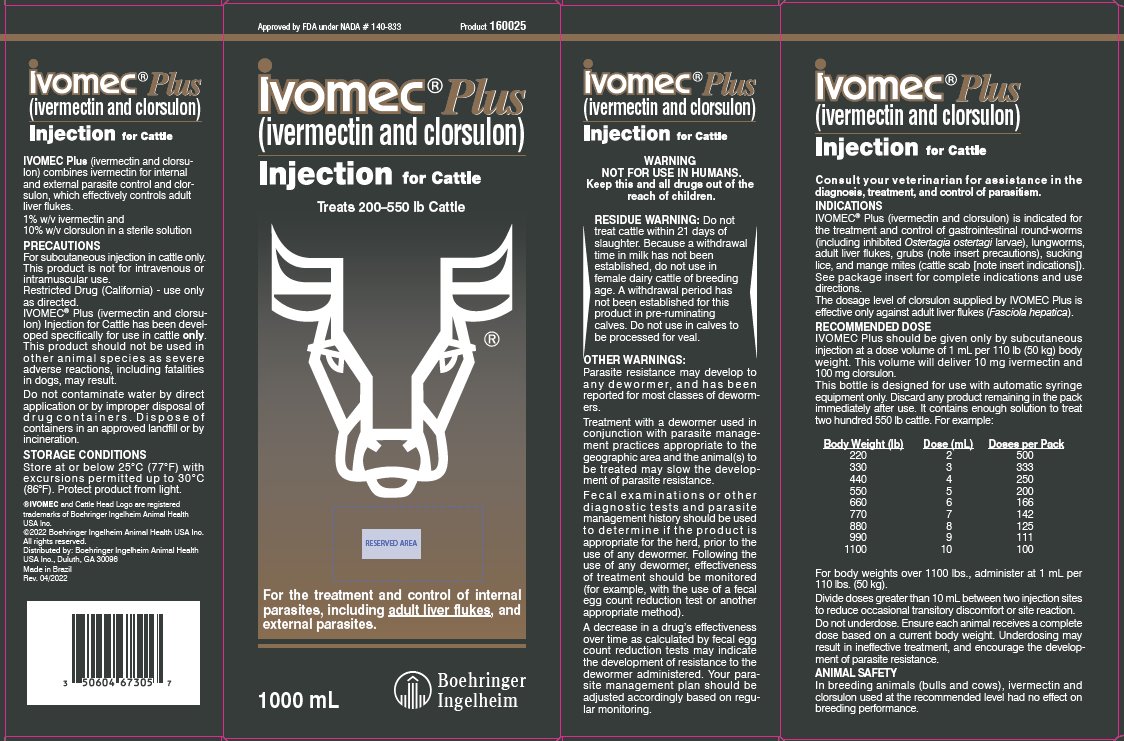 DRUG LABEL: IVOMEC Plus
NDC: 0010-4747 | Form: INJECTION
Manufacturer: Boehringer Ingelheim Animal Health USA Inc.
Category: animal | Type: OTC ANIMAL DRUG LABEL
Date: 20240625

ACTIVE INGREDIENTS: ivermectin 10 mg/1 mL; clorsulon 100 mg/1 mL
INACTIVE INGREDIENTS: glycerol formal; Propylene Glycol

Ivomec® Plus
(ivermectin and clorsulon)
Injection for Cattle

Approved by FDA under NADA # 140-833

160022, 160023, 160024, 160025

VETERINARY INDICATIONS

For the effective treatment and control of internal parasites, including adult liver flukes, and external parasites.

Consult your veterinarian for assistance in the diagnosis, treatment and control of parasitism.

INTRODUCTION

The ability of IVOMEC® (ivermectin) to deliver internal and external parasite control has been proven in cattle markets around the world. Now, Boehringer Ingelheim Animal Health combines ivermectin, the active ingredient of IVOMEC, with clorsulon, an effective adult flukicide. A single injection of IVOMEC Plus (ivermectin and clorsulon) offers all the benefits of IVOMEC plus control of adult Fasciola hepatica.

The dosage level of clorsulon supplied by IVOMEC Plus is effective only against adult liver flukes (Fasciola hepatica).

PRODUCT DESCRIPTION

IVOMEC Plus is a ready-to-use sterile solution containing 1% w/v ivermectin, 10% clorsulon, 40% glycerol formal, and propylene glycol, q.s. ad 100%. It is formulated to deliver the recommended dose level of 200 mcg ivermectin/kg and 2 mg clorsulon/kg given subcutaneously behind the shoulder at the rate of 1 mL per 110 lb (50 kg) body weight.

MODE OF ACTION

Ivermectin is a member of the macrocyclic lactone class of endectocides which have a unique mode of action. Compounds of the class bind selectively and with high affinity to glutamate-gated chloride ion channels which occur in invertebrate nerve and muscle cells. This leads to an increase in the permeability of the cell membrane to chloride ions with hyperpolarization of the nerve or muscle cell, resulting in paralysis and death of the parasite. Compounds of this class may also interact with other ligand-gated chloride channels, such as those gated by the neurotransmitter gamma-aminobutyric acid (GABA).

The margin of safety for compounds of this class is attributable to the fact that mammals do not have glutamate-gated chloride channels, the macrocyclic lactones have a low affinity for other mammalian ligand-gated chloride channels and they do not readily cross the blood-brain barrier. Clorsulon is rapidly absorbed into the circulating blood. Erythrocytes with bound drug as well as plasma are ingested by Fasciola hepatica. Adult Fasciola hepatica are killed by clorsulon because of inhibition of enzymes in the glycolytic pathway, which is their primary source of energy.

INDICATIONS

IVOMEC Plus Injection is indicated for the effective treatment and control of the following parasites of cattle:

Gastrointestinal Roundworms (adults and fourth-stage larvae):
Ostertagia ostertagi (including inhibited O. ostertagi)
O. lyrata
Haemonchus placei
Trichostrongylus axei
T. colubriformis
Cooperia oncophora
C. punctata
C. pectinata
Bunostomum phlebotomum
Nematodirus helvetianus (adults only)
N. spathiger (adults only)
Oesophagostomum radiatum
Lungworms (adults and fourth-stage larvae):
Dictyocaulus viviparus
Liver Flukes:
Fasciola hepatica (adults only)
Cattle Grubs (parasitic stages):
Hypoderma bovis
H. lineatum
Sucking Lice:
Linognathus vituli
Haematopinus eurysternus
Solenopotes capillatus
Mange Mites (cattle scab [Ivermectin has been approved as a scabicide by USDA/APHIS. Federal regulations require that cattle infested with or exposed to scabies (i.e., infestations with Psoroptes ovis) be treated. Ivermectin when used according to label instructions meets this requirement. Treated cattle may be shipped interstate, but they must not be mixed with other cattle for 14 days following treatment. The federal regulations make no restriction on the movement of cattle not affected with or exposed to scabies. However, individual states have additional regulations to govern the interstate shipment of cattle and the regulatory veterinarian in the state of destination should be consulted for applicable regulations on the use of ivermectin in the control of scabies.]):
Psoroptes ovis (syn. P. communis var. bovis)
Sarcoptes scabiei var. bovis

Persistent Activity

IVOMEC Plus Injection has been proved to effectively control infections and to protect cattle from reinfection with Dictyocaulus viviparus and Oesophagostomum radiatum for 28 days after treatment; Ostertagia ostertagi, Trichostrongylus axei and Cooperia punctata for 21 days after treatment; Haemonchus placei, and Cooperia oncophora for 14 days after treatment.

DOSAGE

IVOMEC Plus should be given only by subcutaneous injection at a dose volume of 1 mL per 110 lb (50 kg) body weight. This volume will deliver 10 mg ivermectin and 100 mg clorsulon. For example:

Body Weight (lb) | Dose (mL)
220 | 2
330 | 3
440 | 4
550 | 5
660 | 6
770 | 7
880 | 8
990 | 9
1100 | 10

Do not underdose. Ensure each animal receives a complete dose based on a current body weight. Underdosing may result in ineffective treatment, and encourage the development of parasite resistance.

ADMINISTRATION

IVOMEC Plus (ivermectin and clorsulon) Injection is to be given subcutaneously only. Animals should be appropriately restrained to achieve the proper route of administration. Use of a 16-gauge, 1/2" to 3/4" sterile needle is recommended. Inject the solution subcutaneously (under the skin) behind the shoulder (see illustration).

Any single-dose syringe or standard automatic syringe equipment may be used with the 50 mL bottle. Use the 50 mL bottle within 6 months of first puncture and puncture a maximum of 12 times. If more than 12 punctures are anticipated, the use of multi-dosing equipment is recommended. When using a draw-off spike or needle with bore diameter larger than 16-gauge, discard any product remaining in the bottle immediately after use.

When using the 200 mL, 500 mL or 1000 mL pack size, use only automatic syringe equipment. Discard any product remaining in the pack immediately after use.

Use sterile equipment and sanitize the injection site by applying a suitable disinfectant. Clean, properly disinfected needles should be used to reduce the potential for injection site infections.

No special handling or protective clothing is necessary.

The viscosity of the product increases in cool temperatures.

Administering IVOMEC® Plus at temperatures of 5°C (41°F) or below may be difficult. Users can make dosing easier by warming both the product and injection equipment to about 15°C (59°F).

ANIMAL SAFETY

In breeding animals (bulls and cows), ivermectin and clorsulon used at the recommended level had no effect on breeding performance.

WARNING

NOT FOR USE IN HUMANS.
Keep this and all drugs out of the reach of children.

The Safety Data Sheet (SDS) contains more detailed occupational safety information. To report suspected adverse drug events, for technical assistance, or to obtain a copy of the SDS, contact Boehringer Ingelheim Animal Health USA Inc. at 1-888-637-4251.

RESIDUE WARNING

Do not treat cattle within 21 days of slaughter. Because a withdrawal time in milk has not been established, do not use in female dairy cattle of breeding age. A withdrawal period has not been established for this product in pre-ruminating calves. Do not use in calves to be processed for veal.

PRECAUTIONS

Transitory discomfort has been observed in some cattle following subcutaneous administration. Soft-tissue swelling at the injection site has also been observed. These reactions have disappeared without treatment. Divide doses greater than 10 mL between two injection sites to reduce occasional discomfort or site reaction. Different injection sites should be used for other parenteral products.

IVOMEC Plus Injection has been developed specifically for use in cattle only. This product should not be used in other animal species as severe adverse reactions, including fatalities in dogs, may result.

For subcutaneous injection in cattle only.

This product is not for intravenous or intramuscular use.

Restricted Drug (California) - use only as directed.

When to Treat Cattle with Grubs

IVOMEC Plus effectively controls all stages of cattle grubs. However, proper timing of treatment is important. For most effective results, cattle should be treated as soon as possible after the end of the heel fly (warble fly) season.

Destruction of Hypoderma larvae (cattle grubs) at the period when these grubs are in vital areas may cause undesirable host-parasite reactions including the possibility of fatalities. Killing Hypoderma lineatum when it is in the tissue surrounding the esophagus (gullet) may cause bloat; killing H. bovis when it is in the vertebral canal may cause staggering or paralysis. These reactions are not specific to treatment with IVOMEC Plus, but can occur with any successful treatment of grubs. Cattle should be treated either before or after stages of grub development. Consult your veterinarian concerning the proper time for treatment.

Cattle treated with IVOMEC Plus after the end of the heel fly season may be retreated with ivermectin during the winter for internal parasites, mange mites or sucking lice, without danger of grub-related reactions. A planned parasite control program is recommended.

OTHER WARNINGS:

Parasite resistance may develop to any dewormer, and has been reported for most classes of dewormers.

Treatment with a dewormer used in conjunction with parasite management practices appropriate to the geographic area and the animal(s) to be treated may slow the development of parasite resistance.

Fecal examinations or other diagnostic tests and parasite management history should be used to determine if the product is appropriate for the herd, prior to the use of any dewormer. Following the use of any dewormer, effectiveness of treatment should be monitored (for example, with the use of a fecal egg count reduction test or another appropriate method).

A decrease in a drug's effectiveness over time as calculated by fecal egg count reduction tests may indicate the development of resistance to the dewormer administered. Your parasite management plan should be adjusted accordingly based on regular monitoring.

Environmental Safety

Studies indicate that when ivermectin comes in contact with soil it readily and tightly binds to the soil and becomes inactive overtime. Free ivermectin may adversely affect fish and certain aquatic organisms. Do not permit water runoff from feedlots to enter lakes, streams or ponds. Do not contaminate water by direct application or by improper disposal of drug containers. Dispose of containers in an approved landfill or by incineration.

As with other avermectins, ivermectin is excreted in the dung of treated animals and can inhibit the reproduction and growth of pest and beneficial insects that use dung as a source of food and for reproduction. The magnitude and duration of such effects are species and life-cycle specific.

When used according to label directions, the product is not expected to have an adverse impact on populations of dung-dependent insects.

STORAGE CONDITIONS

Store at or below 25°C (77°F) with excursions permitted up to 30°C (86°F). Protect product from light.

HOW SUPPLIED

IVOMEC Plus Injection is available in four ready-to-use pack sizes:

The 50 mL pack is a multiple-dose, rubber-capped bottle. Each bottle contains sufficient solution to treat 10 head of 550 lb (250 kg) cattle.

The 200 mL pack is a soft, collapsible pack designed for use with automatic syringe equipment. Each pack contains sufficient solution to treat 40 head of 550 lb (250 kg) cattle.

The 500 mL pack is a soft, collapsible pack designed for use with automatic syringe equipment. Each pack contains sufficient solution to treat 100 head of 550 lb (250 kg) cattle.

The 1000 mL pack is a soft, collapsible pack designed for use with automatic syringe equipment. Each pack contains sufficient solution to treat 200 head of 550 lb (250 kg) cattle.

®IVOMEC and Cattle Head Logo are registered trademarks of Boehringer Ingelheim Animal Health USA Inc.

© 2022 Boehringer Ingelheim Animal Health USA Inc. All rights reserved.

Distributed by:
Boehringer Ingelheim Animal Health USA Inc.
Duluth, GA 30096

Made in Brazil

Rev. 04/2022 4030364

156264-004

PRINCIPAL DISPLAY PANEL - 1000 mL Display Carton

1000 mL